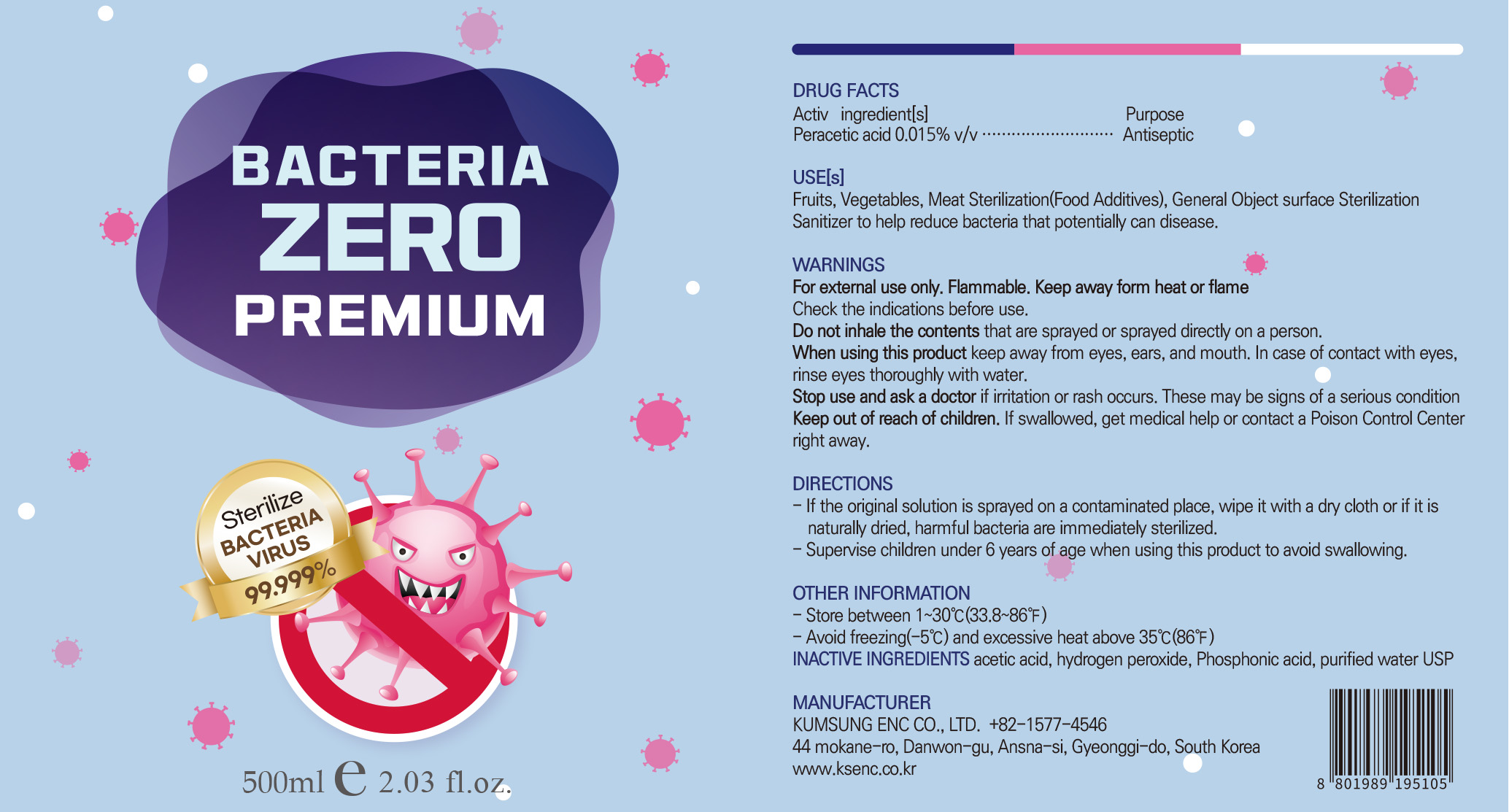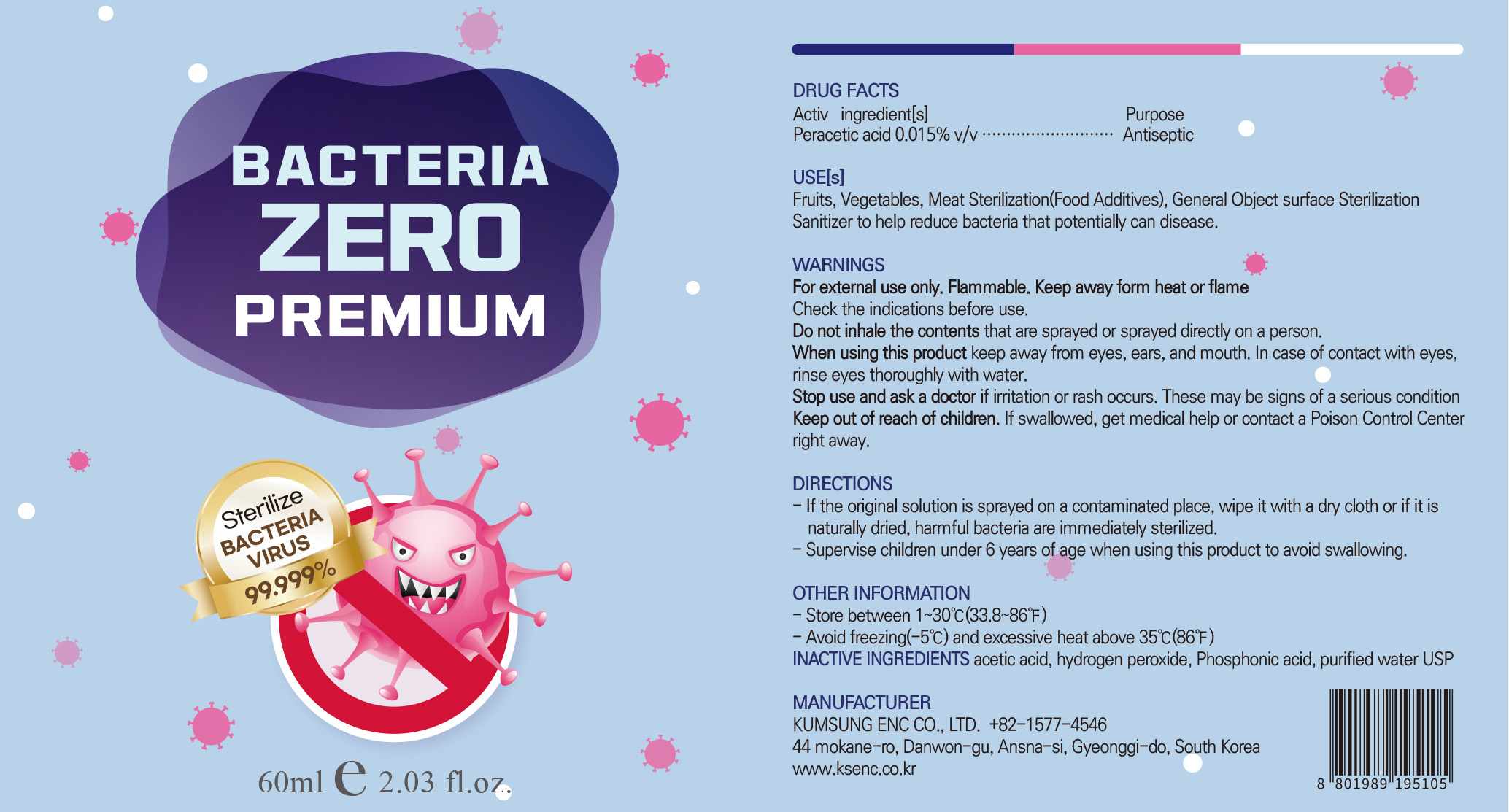 DRUG LABEL: BACTERIA ZERO PREMIUM
NDC: 80138-204 | Form: LIQUID
Manufacturer: KUMSUNG E&C CO., LTD
Category: otc | Type: HUMAN OTC DRUG LABEL
Date: 20220101

ACTIVE INGREDIENTS: PERACETIC ACID 0.015 g/100 mL
INACTIVE INGREDIENTS: PHOSPHOROUS ACID; HYDROGEN PEROXIDE; WATER; ACETIC ACID

80138-204 BACTERIA ZERO PREMIUM

Active Ingredient[s]

Peracetic acid 0.015%

Purpose

Antiseptic

USE[s]

Fruits, Vegetables, Meat Sterilization(Food Additives), General Object surface Sterilization
Sanitizer to help reduce bacteria that potentially can disease.

WARNINGS

For external use only. Flammable. Keep away form heat or flame
Check the indications before use.
Do not inhale the contents that are sprayed or sprayed directly on a person.

When using this product

keep away from eyes, ears, and mouth. In case of contact with eyes, rinse eyes thoroughly with water.

Stop use and ask a doctor

if irritation or rash occurs. These may be signs of a serious condition

Keep out of reach of children.

If swallowed, get medical help or contact a Poison Control Center right away.

DIRECTIONS

- If the original solution is sprayed on a contaminated place, wipe it with a dry cloth or if it is naturally dried, harmful bacteria are immediately sterilized.
- Supervise children under 6 years of age when using this product to avoid swallowing.

OTHER INFORMATION

- Store between 1~30℃(33.8~86℉)
- Avoid freezing(-5℃) and excessive heat above 35℃(86℉)

INACTIVE INGREDIENTS

acetic acid, hydrogen peroxide, Phosphonic acid, purified water USP